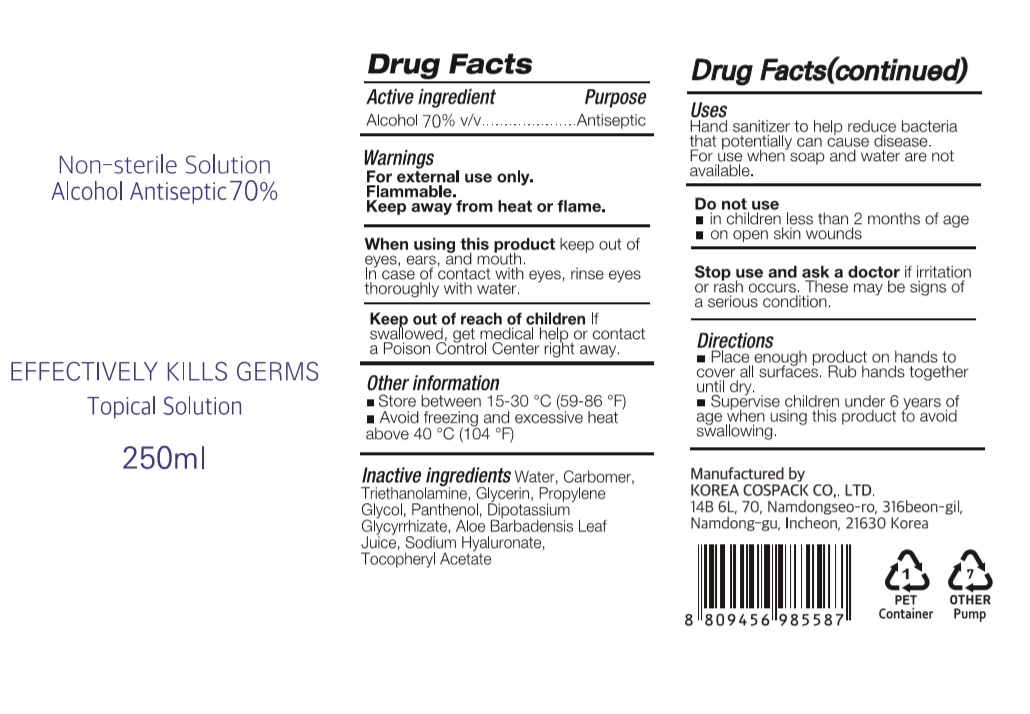 DRUG LABEL: CLEAN TO CLEAN HAND SANITIZER Gel PLUS
NDC: 74064-2571 | Form: GEL
Manufacturer: KOREA COSPACK CO.,LTD.
Category: otc | Type: HUMAN OTC DRUG LABEL
Date: 20200526

ACTIVE INGREDIENTS: ALCOHOL 175 mL/250 mL
INACTIVE INGREDIENTS: .ALPHA.-TOCOPHEROL ACETATE; HYALURONATE SODIUM; TROLAMINE; GLYCERIN; CARBOMER HOMOPOLYMER, UNSPECIFIED TYPE; WATER; PROPYLENE GLYCOL; PANTHENOL; GLYCYRRHIZINATE DIPOTASSIUM; ALOE VERA LEAF

CLEAN TO CLEAN HAND SANITIZER GEL PLUS 250 ml BOTTLE+PUMP
74064-2571-1